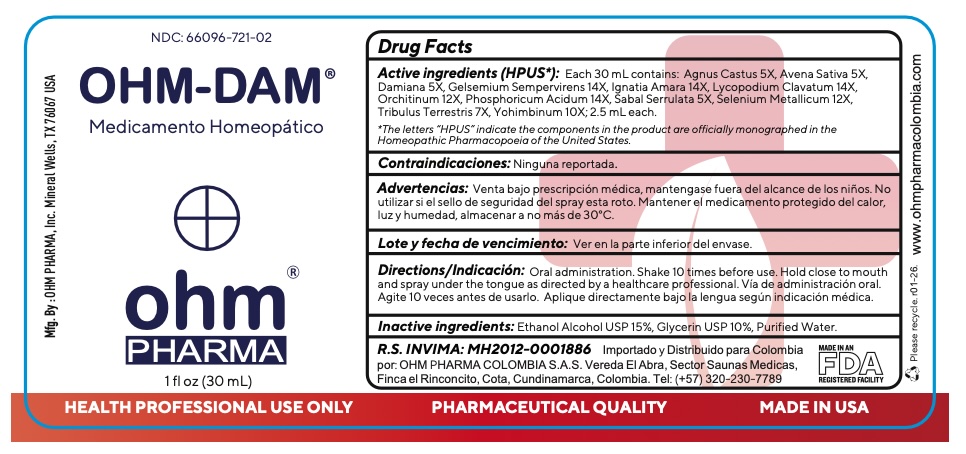 DRUG LABEL: OHM-DAM
NDC: 66096-721 | Form: SPRAY
Manufacturer: OHM PHARMA INC.
Category: homeopathic | Type: HUMAN OTC DRUG LABEL
Date: 20260128

ACTIVE INGREDIENTS: TURNERA DIFFUSA LEAFY TWIG 5 [hp_X]/30 mL; GELSEMIUM SEMPERVIRENS ROOT 14 [hp_X]/30 mL; STRYCHNOS IGNATII SEED 14 [hp_X]/30 mL; LYCOPODIUM CLAVATUM SPORE 14 [hp_X]/30 mL; BOS TAURUS TESTICLE 12 [hp_X]/30 mL; PHOSPHORIC ACID 14 [hp_X]/30 mL; SAW PALMETTO 5 [hp_X]/30 mL; SELENIUM 12 [hp_X]/30 mL; TRIBULUS TERRESTRIS WHOLE 7 [hp_X]/30 mL; YOHIMBINE 10 [hp_X]/30 mL; CHASTE TREE FRUIT 5 [hp_X]/30 mL; AVENA SATIVA FLOWERING TOP 5 [hp_X]/30 mL
INACTIVE INGREDIENTS: ALCOHOL; GLYCERIN; WATER

OHM-DAM

ACTIVE INGREDIENT

Active ingredients (HPUS*):Each 100 mL contains: Agnus Castus 5X, Avena Sativa 5X,
Damiana 5X, Gelsemium Sempervirens 14X, Ignatia Amara 14X, Lycopodium Clavatum 14X,
Orchitinum 12X, Phosphoricum Acidum 14X, Sabal Serrulata 5X, Selenium Metallicum 12X,
Tribulus Terrestris 7X, Yohimbinum 10X; 2.50 mL each.

*The letters “HPUS” indicate the components in the product are officially monographed in the
Homeopathic Pharmacopoeia of the United States.

INDICATIONS AND USAGE

Contraindicaciones:Ninguna reportada.

WARNINGS

Advertencias:Venta bajo prescripción médica, mantengase fuera del alcance de los niños. No
utilizar si el sello de seguridad del spray esta roto. Mantener el medicamento protegido del calor,
luz y humedad, almacenar a no más de 30°C.

KEEP OUT OF REACH OF CHILDREN

Mantengase fuera del alcance de los niños.

DOSAGE AND ADMINISTRATION

Directions/Indicación:Oral administration. Shake 10 times before use. Hold close to mouth
and spray under the tongue as directed by a healthcare professional. Vía de administración oral.
Agite 10 veces antes de usarlo. Aplique directamente bajo la lengua según indicación médica.

INACTIVE INGREDIENT

Inactive ingredients:Ethanol Alcohol USP 15%, Glycerin USP 10%, Purified Water.

OTHER SAFETY INFORMATION

Lote y fecha de vencimiento:Ver en la parte inferior del envase.

QUESTIONS

R.S. INVIMA: MH2012-0001886

Importado y distribuido para Colombia por
OHM PHARMA COLOMBIA SAS
Vereda El Abra
Sector Saunas Medicas
Finca el Rinconcito
Cota, Cundinamarca, Colombia
Tel: (+57) 320-230-7789

Mfg. By : OHM PHARMA, Inc.
Mineral Wells, TX 76067 USA
www.ohmpharma.com

PACKAGE LABEL

NDC: 66096-721-02

OHM-DAM

Medicamento Homeopatico

ohm

PHARMA

1 fl oz (30 mL)

PURPOSE

Medicamento Homeopático